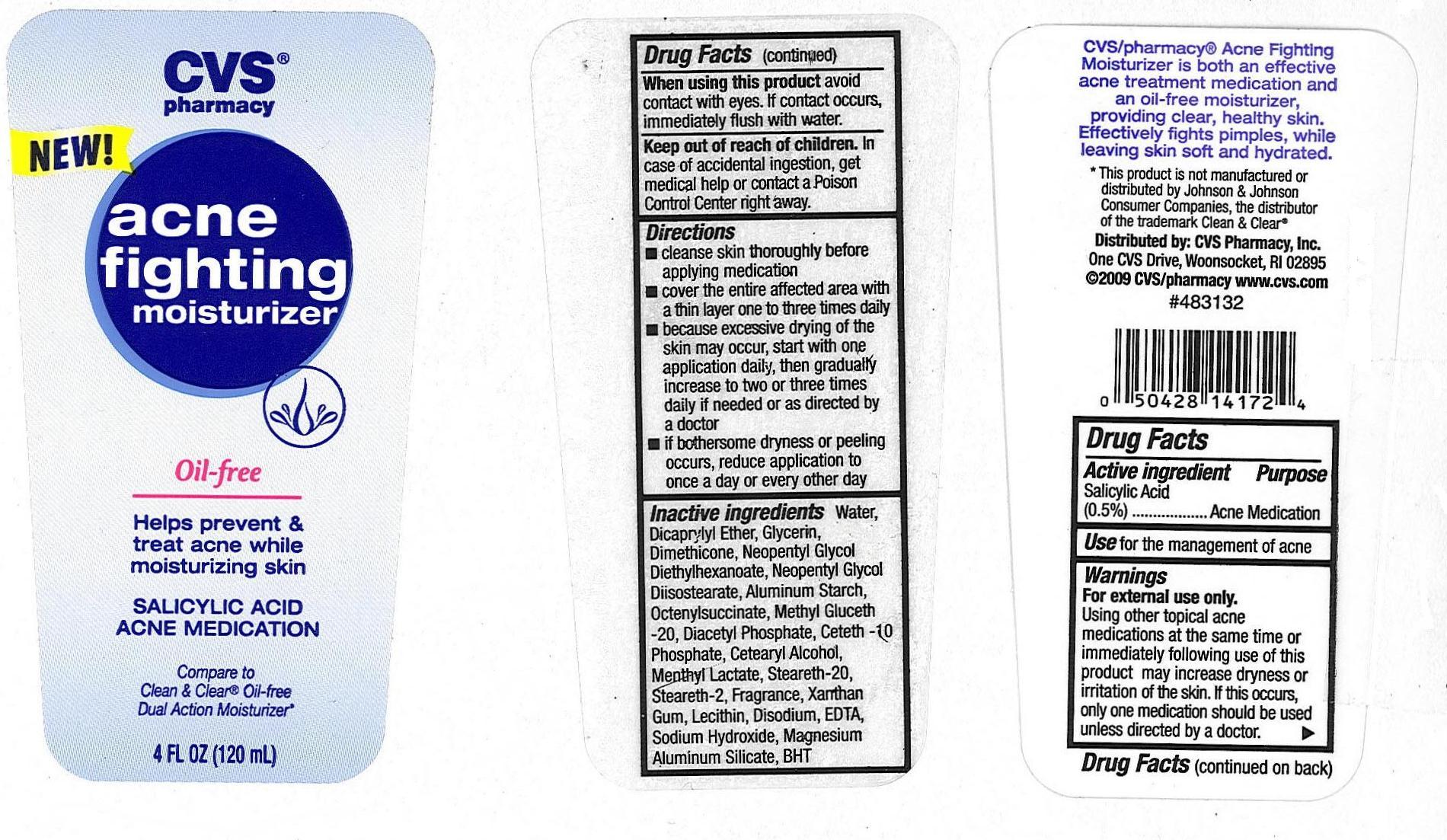 DRUG LABEL: SALICYLIC ACID
NDC: 59779-078 | Form: LIQUID
Manufacturer: CVS
Category: otc | Type: HUMAN OTC DRUG LABEL
Date: 20110216

ACTIVE INGREDIENTS: SALICYLIC ACID 5 mg/1 mL
INACTIVE INGREDIENTS: Water; DICAPRYLYL ETHER; DIMETHICONE; SODIUM LAURYL SULFATE; ALUMINUM STARCH OCTENYLSUCCINATE; CETOSTEARYL ALCOHOL; METHYL GLUCETH-20; METHYLCHLOROISOTHIAZOLINONE; MENTHYL LACTATE; STEARETH-20; XANTHAN GUM; LECITHIN, SOYBEAN; EDETATE DISODIUM; SODIUM HYDROXIDE; MAGNESIUM ALUMINUM SILICATE; BUTYLATED HYDROXYTOLUENE

drug facts

Active ingredient Purpose
Salicylic Acid
(0.5%)....................................Acne Medication

Active ingredient Purpose
Salicylic Acid
(0.5%)..............................Acne Medication
______________________________________
Use for the management of acne

KEEP OUT OF REACH OF CHILDREN

_______________________________
Keep out of reach of children. In
case of accidental ingestion, get
medical help or contact a Poison
Control Center right away.

INDICATIONS AND USAGE

Use for the management of acne
_______________________________
Directions
- Cleanse skin thoroughly before
applying medication
- cover the entire affected area with
a thin layer one to two times daily
- because excessive drying of the
skin may occur, start with one
application daily, then gradually
increase to two or three times
daily if needed or as directed by
a doctor
- if bothersome dryness or peeling
occurs, reduce application to
once a day or every other day

Warnings
For external use only.
Using other topical acne
medications at the same time or
immediately following use of this
product may increase dryness or
irritation of the skin. If this occurs,
only one medication should be used
unless directed by a doctor.
______________________________
When using this product avoid
contact with eyes. If contact occurs,
immediately flush with water.
_______________________________
Keep out of reach of children. In
case of accidental ingestion, get
medical help or contact a Poison
Control Center right away.

Directions
- Cleanse skin thoroughly before
applying medication
- cover the entire affected area with
a thin layer one to two times daily
- because excessive drying of the
skin may occur, start with one
application daily, then gradually
increase to two or three times
daily if needed or as directed by
a doctor
- if bothersome dryness or peeling
occurs, reduce application to
once a day or every other day

Inactive Ingredients Water,
Dicaprylyl Ether, Glycerin,
Dimethicone, Neopentyl Glycol
Diethylhexanonate, Neopentyl Glycol
Diisostearate, Aluminum Starch,
Octenylsuccinate, Methyl Gluceth
-20, Diacetyl Phosphate, Ceteth-10
Phosphate, Cetearyl Alcohol,
Menthyl Lactate, Steareth-20,
Steareth-2, Fragrance, Xanthan
Gum, Lecithin, Disodium EDTA,
Sodium Hydroxide, Magnesium
Aluminum Silicate, BHT